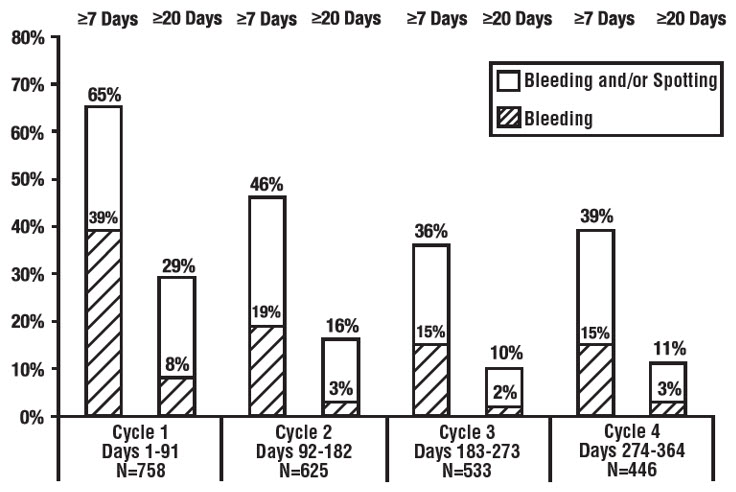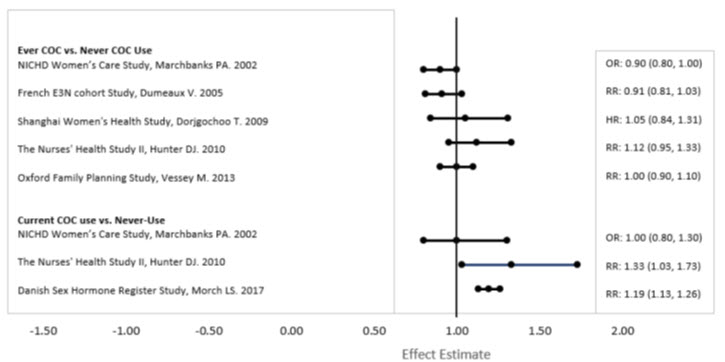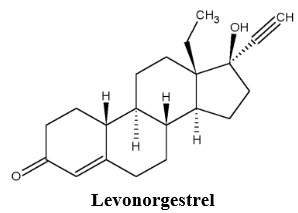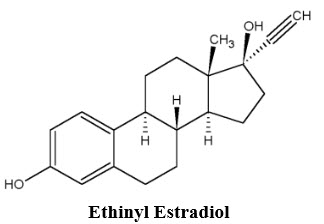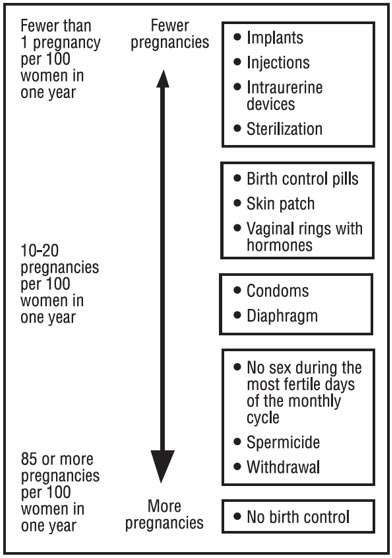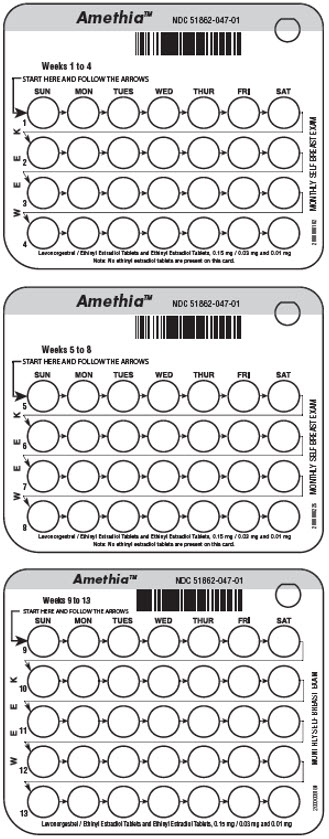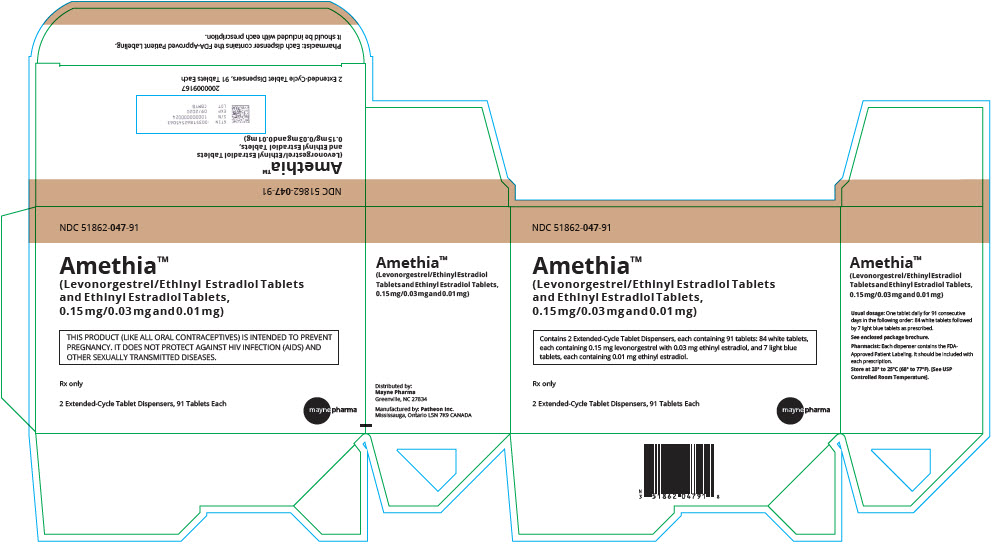 DRUG LABEL: Amethia
NDC: 51862-047 | Form: KIT | Route: ORAL
Manufacturer: Mayne Pharma Inc
Category: prescription | Type: HUMAN PRESCRIPTION DRUG LABEL
Date: 20240301

ACTIVE INGREDIENTS: ETHINYL ESTRADIOL 0.03 mg/1 1; LEVONORGESTREL 0.15 mg/1 1; ETHINYL ESTRADIOL 0.01 mg/1 1
INACTIVE INGREDIENTS: LACTOSE MONOHYDRATE; MICROCRYSTALLINE CELLULOSE; POVIDONE, UNSPECIFIED; CROSCARMELLOSE SODIUM; MAGNESIUM STEARATE; .ALPHA.-TOCOPHEROL; ANHYDROUS LACTOSE; POVIDONE, UNSPECIFIED; FD&C BLUE NO. 1; SILICON DIOXIDE; STARCH, CORN; STEARIC ACID

HIGHLIGHTS OF PRESCRIBING INFORMATION

These highlights do not include all the information needed to use AMETHIA tablets safely and effectively. See full prescribing information for AMETHIA tablets.
AMETHIA - Levonorgestrel/Ethinyl Estradiol tablets and Ethinyl Estradiol tablets for oral use.
Initial U.S. Approval: 1982

WARNING: CIGARETTE SMOKING AND SERIOUS CARDIOVASCULAR EVENTS

See full prescribing information for complete boxed warning.

- Women who are over 35 years old and smoke should not use AMETHIA tablets.
- Cigarette smoking increases the risk of serious cardiovascular events from combination oral contraceptive (COC) use.

RECENT MAJOR CHANGES

Warnings, Precautions, Malignant Neoplasms (5.2) | 04/2022

1. INDICATIONS AND USAGE

AMETHIA tablets are an estrogen/progestin COC indicated for use by women to prevent pregnancy. (1)

2. DOSAGE AND ADMINISTRATION

Take one tablet daily by mouth at the same time every day for 91 days. (2)

3. DOSAGE FORMS AND STRENGTHS

AMETHIA tablets consists of 84 white tablets containing 0.15 mg levonorgestrel and 0.03 mg ethinyl estradiol, and 7 light blue tablets containing 0.01 mg ethinyl estradiol. (3)

4. CONTRAINDICATIONS

- A high risk of arterial or venous thrombotic diseases (4)
- Undiagnosed abnormal genital bleeding (4)
- Breast cancer or other estrogen- or progestin-sensitive cancer (4)
- Liver tumors or liver disease (4)
- Pregnancy (4)
- Co-administration with Hepatitis C drug combinations containing ombitasvir/paritaprevir/ritonavir, with or without dasabuvir (4)

5. WARNINGS AND PRECAUTIONS

- Vascular risks: Stop AMETHIA tablets if a thrombotic event occurs. Stop AMETHIA tablets at least 4 weeks before and through 2 weeks after major surgery. Start AMETHIA tablets no earlier than 4 weeks after delivery, in women who are not breastfeeding. (5.1)
- Liver disease: Discontinue AMETHIA tablets if jaundice occurs. (5.3)
- High blood pressure: Do not prescribe AMETHIA tablets for women with uncontrolled hypertension or hypertension with vascular disease. (5.5)
- Carbohydrate and lipid metabolic effects: Monitor prediabetic and diabetic women taking AMETHIA tablets. Consider an alternate contraceptive method for women with uncontrolled dyslipidemias. (5.7)
- Headache: Evaluate significant change in headaches and discontinue AMETHIA tablets if indicated. (5.8)
- Uterine bleeding: Evaluate irregular bleeding or amenorrhea (5.9)

6. ADVERSE REACTIONS

The most common adverse reactions (≥5%) in clinical trials for levonorgestrel/ethinyl estradiol tablets and ethinyl estradiol tablets are irregular and/or heavy uterine bleeding, weight gain, and acne. (6)

To report SUSPECTED ADVERSE REACTIONS, contact Mayne Pharma. at 1-844 -825-8500 or FDA at 1-800-FDA-1088 or www.fda.gov/medwatch.

7. DRUG INTERACTIONS

Drugs or herbal products that induce certain enzymes, including CYP3A4, may decrease the effectiveness of COCs or increase breakthrough bleeding. Counsel patients to use a back-up method or alternative method of contraception when enzyme inducers are used with COCs. (7.1)

8. USE IN SPECIFIC POPULATIONS

- Nursing Mothers: Not recommended for nursing mothers; can decrease milk production. (8.3)

FULL PRESCRIBING INFORMATION

WARNING: CIGARETTE SMOKING AND SERIOUS CARDIOVASCULAR EVENTS

Cigarette smoking increases the risk of serious cardiovascular events from combination oral contraceptives (COC) use. This risk increases with age, particularly in women over 35 years of age, and with the number of cigarettes smoked. For this reason, COCs should not be used by women who are over 35 years of age and smoke.[See Contraindications (4).]

1. INDICATIONS AND USAGE

AMETHIA tablets are indicated for use by women to prevent pregnancy.

2. DOSAGE AND ADMINISTRATION

Take one tablet by mouth at the same time every day. The dosage of AMETHIA tablets is one white tablet containing levonorgestrel and ethinyl estradiol daily for 84 consecutive days, followed by one light blue ethinyl estradiol tablet for 7 days. To achieve maximum contraceptive effectiveness, AMETHIA tablets must be taken exactly as directed and at intervals not exceeding 24 hours.

Instruct the patient to begin taking AMETHIA tablets on the first Sunday after the onset of menstruation. If menstruation begins on a Sunday, the first white tablet is taken that day. One white tablet should be taken daily for 84 consecutive days, followed by one light blue tablet for 7 consecutive days. A non-hormonal back-up method of contraception (such as condoms or spermicide) should be used until a white tablet has been taken daily for 7 consecutive days. A scheduled period should occur during the 7 days that the light blue tablets are taken.

Begin the next and all subsequent 91-day cycles without interruption on the same day of the week (Sunday) on which the patient began her first dose of AMETHIA tablets, following the same schedule: 84 days taking a white tablet followed by 7 days taking a blue tablet. If the patient does not immediately start her next pill pack, she should protect herself from pregnancy by using a non-hormonal back-up method of contraception until she has taken a white tablet daily for 7 consecutive days.

If unscheduled spotting or bleeding occurs, instruct the patient to continue on the same regimen. If the bleeding is persistent or prolonged, advise the patient to consult her healthcare provider.

For patient instructions regarding missed pills, see FDA-Approved Patient Labeling.

For postpartum women who are not breastfeeding, start AMETHIA tablets no earlier than four to six weeks postpartum due to increased risk of thromboembolism. If the patient starts on AMETHIA tablets postpartum and has not yet had a period, evaluate for possible pregnancy, and instruct her to use an additional method of contraception until she has taken a white tablet for 7 consecutive days.

3. DOSAGE FORMS AND STRENGTHS

AMETHIA tablets are available in Extended-Cycle Tablet Dispensers, each containing a 13-week supply of tablets: 84 white tablets, each containing 0.15 mg of levonorgestrel and 0.03 mg ethinyl estradiol, and 7 light blue tablets each containing 0.01 mg of ethinyl estradiol. The white tablets are round, flat face beveled edge, unscored tablets with WATSONon one side and 268on the other side. The light blue tablets are round, flat face beveled edge, unscored tablets with WATSONon one side and 270on the other side.

4. CONTRAINDICATIONS

AMETHIA tablets are contraindicated in females who are known to have or develop the following conditions:

- A high risk of arterial or venous thrombotic diseases. Examples include women who are known to:
  1. Smoke, if over age 35 [see Boxed Warningand Warnings and Precautions (5.1)] .
  2. Have deep vein thrombosis or pulmonary embolism, now or in the past [see Warnings and Precautions (5.1)] .
  3. Have cerebrovascular disease [see Warnings and Precautions (5.1)].
  4. Have coronary artery disease [see Warnings and Precautions (5.1)] .
  5. Have thrombogenic valvular or thrombogenic rhythm diseases of the heart (for example, subacute bacterial endocarditis with valvular disease, or atrial fibrillation) [see Warnings and Precautions (5.1)] .
  6. Have inherited or acquired hypercoagulopathies [see Warnings and Precautions (5.1)] .
  7. Have uncontrolled hypertension [see Warnings and Precautions (5.5)] .
  8. Have diabetes with vascular disease [see Warnings and Precautions (5.7)] .
  9. Have headaches with focal neurological symptoms or have migraine headaches with or without aura if over age 35 [see Warnings and Precautions (5.8)] .
- Undiagnosed abnormal genital bleeding [see Warnings and Precautions (5.9)] .
- Current diagnosis of, or history of, breast cancer, which may be hormone-sensitive [see Warnings and Precautions (5.2)] .
- Liver tumors, benign or malignant, or liver disease [see Warnings and Precautions (5.3)and Use in Specific Populations (8.6)] .
- Pregnancy, because there is no reason to use COCs during pregnancy [see Warnings and Precautions (5.10)and Use in Specific Populations (8.1)] .
- Use of Hepatitis C drug combinations containing ombitasvir/paritaprevir/ritonavir, with or without dasabuvir, due to the potential for ALT elevations [see Warnings and Precautions (5.4)].

5. WARNINGS AND PRECAUTIONS

5.1 Thrombotic and Other Vascular Events

Stop AMETHIA tablets if an arterial or deep venous thrombotic event occurs. Although the use of COCs increases the risk of venous thromboembolism, pregnancy increases the risk of venous thromboembolism as much or more than the use of COCs. The risk of venous thromboembolism in women using COCs is 3 to 9 per 10,000 woman-years. The excess risk is highest during the first year of use of a COC. Use of COCs also increases the risk of arterial thromboses such as strokes and myocardial infarctions, especially in women with other risk factors for these events. The risk of thromboembolic disease due to COCs gradually disappears after COC use is discontinued.

Use of AMETHIA tablets provides women with more hormonal exposure on a yearly basis than conventional monthly oral contraceptives containing the same strength synthetic estrogens and progestins (an additional 9 and 13 weeks of exposure to progestin and estrogen, respectively, per year).

If feasible, stop AMETHIA tablets at least 4 weeks before and through 2 weeks after major surgery or other surgeries known to have an elevated risk of thromboembolism.

Start AMETHIA tablets no earlier than 4 - 6 weeks after delivery, in women who are not breastfeeding. The risk of postpartum thromboembolism decreases after the third postpartum week, whereas the risk of ovulation increases after the third postpartum week.

COCs have been shown to increase both the relative and attributable risks of cerebrovascular events (thrombotic and hemorrhagic strokes), although, in general, the risk is greatest among older (>35 years of age), and hypertensive women who also smoke. COCs also increase the risk for stroke in women with other underlying risk factors.

Oral contraceptives must be used with caution in women with cardiovascular disease risk factors.

Stop AMETHIA tablets if there is unexplained loss of vision, proptosis, diplopia, papilledema, or retinal vascular lesions. Evaluate for retinal vein thrombosis immediately.

5.2 Malignant Neoplasms

Breast Cancer

AMETHIA tablets are contraindicated in females who currently have or have had breast cancer because breast cancer may be hormonally sensitive [see Contraindications (4)].

Epidemiology studies have not found a consistent association between use of combined oral contraceptives (COCs) and breast cancer risk. Studies do not show an association between ever (current or past) use of COCs and risk of breast cancer. However, some studies report a small increase in the risk of breast cancer among current or recent users (<6 months since last use) and current users with longer duration of COC use [see Postmarketing Experience (6.2)].

Cervical Cancer

Some studies suggest that COCs are associated with an increase in the risk of cervical cancer or intraepithelial neoplasia. However, there is controversy about the extent to which these findings are due to differences in sexual behavior and other factors.

5.3 Liver Disease

Discontinue AMETHIA tablets if jaundice develops. Steroid hormones may be poorly metabolized in patients with impaired liver function. Acute or chronic disturbances of liver function may necessitate the discontinuation of COC use until markers of liver function return to normal and COC causation has been excluded.

Hepatic adenomas are associated with COC use. An estimate of the attributable risk is 3.3 cases/100,000 COC users. Rupture of hepatic adenomas may cause death through intra-abdominal hemorrhage.

Studies have shown an increased risk of developing hepatocellular carcinoma in long-term (> 8 years) COC users. However, the attributable risk of liver cancers in COC users is less than one case per million users.

Oral contraceptive-related cholestasis may occur in women with a history of pregnancy-related cholestasis. Women with a history of COC-related cholestasis may have the condition recur with subsequent COC use.

5.4 Risk of Liver Enzyme Elevations with Concomitant Hepatitis C Treatment

During clinical trials with the Hepatitis C combination drug regimen that contains ombitasvir/paritaprevir/ritonavir, with or without dasabuvir, ALT elevations greater than 5 times the upper limit of normal (ULN), including some cases greater than 20 times the ULN, were significantly more frequent in women using ethinyl estradiol-containing medications, such as COCs. Discontinue AMETHIA tablets prior to starting therapy with the combination drug regimen ombitasvir/paritaprevir/ritonavir, with or without dasabuvir [see Contraindications (4)] . AMETHIA tablets can be restarted approximately 2 weeks following completion of treatment with the Hepatitis C combination drug regimen.

5.5 High Blood Pressure

For women with well-controlled hypertension, monitor blood pressure and stop AMETHIA tablets if blood pressure rises significantly. Women with uncontrolled hypertension or hypertension with vascular disease should not use COCs.

An increase in blood pressure has been reported in women taking COCs, and this increase is more likely in older women and with extended duration of use. The incidence of hypertension increases with increasing concentration of progestin.

5.6 Gallbladder Disease

Studies suggest a small increased relative risk of developing gallbladder disease among COC users.

5.7 Carbohydrate and Lipid Metabolic Effects

Carefully monitor prediabetic and diabetic women who are taking AMETHIA tablets. COCs may decrease glucose tolerance in a dose-related fashion.

Consider alternative contraception for women with uncontrolled dyslipidemias. A small proportion of women will have adverse lipid changes while on COCs.

Women with hypertriglyceridemia, or a family history thereof, may be at an increased risk of pancreatitis when using COCs.

5.8 Headache

If a woman taking AMETHIA tablets develops new headaches that are recurrent, persistent, or severe, evaluate the cause and discontinue Levonorgestrel/Ethinyl Estradiol tablets and Ethinyl Estradiol tablets if indicated.

An increase in frequency or severity of migraine during COC use (which may be prodromal of a cerebrovascular event) may be a reason for immediate discontinuation of the COC.

5.9 Bleeding Irregularities

Unscheduled (breakthrough) bleeding and spotting sometimes occur in patients on COCs, especially during the first 3 months of use. If bleeding persists, check for causes such as pregnancy or malignancy.

If pathology and pregnancy are excluded, bleeding irregularities may resolve over time or with a change to a different COC.

When prescribing AMETHIA tablets, the convenience of fewer planned menses (4 per year instead of 13 per year) should be weighed against the inconvenience of increased unscheduled bleeding and/or spotting. The primary clinical trial (PSE-301) that evaluated the efficacy of levonorgestrel/ethinyl estradiol tablets and ethinyl estradiol tablets also assessed unscheduled bleeding. The participants in the 12-month clinical trial (N=1,006) completed the equivalent of 8,681 28-day cycles of exposure and were composed primarily of women who had used oral contraceptives previously (89%) as opposed to new users (11%). A total of 82 (8.2%) of the women discontinued levonorgestrel/ethinyl estradiol tablets and ethinyl estradiol tablets, at least in part, due to bleeding or spotting.

Scheduled (withdrawal) bleeding and/or spotting remained fairly constant over time, with an average of 3 days of bleeding and/or spotting per each 91-day cycle. Unscheduled bleeding and unscheduled spotting decreased over successive 91-day cycles. Table 1 below presents the number of days with unscheduled bleeding in treatment cycles 1 and 4. Table 2 presents the number of days with unscheduled spotting in treatment cycles 1 and 4.

Table 1: Total Number of Days with Unscheduled Bleeding
91-Day Treatment Cycle | Days per 84-Day Interval |  |  |  | Days per 28-Day Interval
 | Q1 | Median | Q3 | Mean | Mean
1st | 1 | 4 | 10 | 6.9 | 1.7
4th | 0 | 1 | 4 | 3.2 | 0.8
Q1=Quartile 1: 25% of women had this number of days of unscheduled bleeding
Median: 50% of women had ≤ this number of days of unscheduled bleeding
Q3=Quartile 3: 75% of women had ≤ this number of days of unscheduled bleeding

Table 2: Total Number of Days with Unscheduled Spotting
91-Day Treatment Cycle | Days per 84-Day Interval |  |  |  | Days per 28-Day Interval
 | Q1 | Median | Q3 | Mean | Mean
1st | 1 | 4 | 11 | 7.4 | 1.9
4th | 0 | 2 | 7 | 4.4 | 1.1
Q1=Quartile 1: 25% of women had ≤ this number of days of unscheduled spotting
Median: 50% of women had ≤ this number of days of unscheduled spotting
Q3=Quartile 3: 75% of women had ≤ this number of days of unscheduled spotting

Figure 1 shows the percentage of levonorgestrel/ethinyl estradiol tablets and ethinyl estradiol tablets subjects participating in trial PSE-301 with ≥ 7 days or ≥ 20 days of unscheduled bleeding and/or spotting, or only unscheduled bleeding, during each 91-day treatment cycle.

Figure 1: Percent of Women Taking Levonorgestrel and Ethinyl Estradiol Tablets and Ethinyl Estradiol Tablets who Reported Unscheduled Bleeding and/or Spotting or only Unscheduled Bleeding

Amenorrhea sometimes occurs in women who are using COCs. Pregnancy should be ruled out in the event of amenorrhea. Some women may encounter amenorrhea or oligomenorrhea after stopping COCs, especially when such a condition was pre-existent.

5.10 COC Use Before or During Early Pregnancy

Extensive epidemiological studies have revealed no increased risk of birth defects in women who have used oral contraceptives prior to pregnancy. Studies also do not suggest a teratogenic effect, particularly in so far as cardiac anomalies and limb-reduction defects are concerned, when taken inadvertently during early pregnancy. Oral contraceptive use should be discontinued if pregnancy is confirmed.

The administration of oral contraceptives to induce withdrawal bleeding should not be used as a test for pregnancy [see Use in Specific Populations (8.1)] .

5.11 Emotional Disorders

Women with a history of depression should be carefully observed and AMETHIA tablets discontinued if depression recurs to a serious degree.

5.12 Interference with Laboratory Tests

The use of COCs may change the results of some laboratory tests, such as coagulation factors, lipids, glucose tolerance, and binding proteins. Women on thyroid hormone replacement therapy may need increased doses of thyroid hormone because serum concentrations of thyroid binding globulin increase with use of COCs.

5.13 Monitoring

A woman who is taking COCs should have a yearly visit with her healthcare provider for a blood pressure check and for other indicated health care.

5.14 Other Conditions

In women with hereditary angioedema, exogenous estrogens may induce or exacerbate symptoms of angioedema. Chloasma may occasionally occur, especially in women with a history of chloasma gravidarum. Women with a tendency to chloasma should avoid exposure to the sun or ultraviolet radiation while taking COCs.

6. ADVERSE REACTIONS

The following serious adverse reactions with the use of COCs are discussed elsewhere in the labeling:

- Serious cardiovascular events and smoking [see Boxed Warningand Warnings and Precautions (5.1)]
- Vascular events [see Warnings and Precautions (5.1)]
- Liver disease [see Warnings and Precautions (5.3)]

Adverse reactions commonly reported by COC users are:

- Irregular uterine bleeding
- Nausea
- Breast tenderness
- Headache

6.1 Clinical Trial Experience

Because clinical trials are conducted under widely varying conditions, adverse reaction rates observed in the clinical trials of a drug cannot be directly compared to the rates in the clinical trials of another drug and may not reflect the rates observed in practice.

The clinical trial that evaluated the safety and efficacy of levonorgestrel/ethinyl estradiol tablets and ethinyl estradiol tablets was a 12-month, randomized, multicenter, open-label study, which enrolled women aged 18-40, of whom 1,006 took at least one dose of levonorgestrel/ethinyl estradiol tablets and ethinyl estradiol tablets.

Adverse Reactions Leading to Study Discontinuation: 16.3% of the women discontinued from the clinical trial due to an adverse reaction; the most common adverse reactions (≥ 1% of women) leading to discontinuation were irregular and/or heavy uterine bleeding (5.9%), weight gain (2.4%), mood changes (1.5%), and acne (1.0%).

Common Treatment-Emergent Adverse Reactions (≥ 5% of women): irregular and/or heavy uterine bleeding (17%), weight gain (5%), acne (5%).

Serious Adverse Reactions:migraine, cholecystitis, cholelithiasis, pancreatitis, abdominal pain, and major depressive disorder.

6.2 Postmarketing Experience

Five studies that compared breast cancer risk between ever-users (current or past use) of COCs and never-users of COCs reported no association between ever use of COCs and breast cancer risk, with effect estimates ranging from 0.90–1.12 (Figure 2).

Three studies compared breast cancer risk between current or recent COC users (<6 months since last use) and never users of COCs (Figure 2). One of these studies reported no association between breast cancer risk and COC use. The other two studies found an increased relative risk of 1.19–1.33 with current or recent use. Both of these studies found an increased risk of breast cancer with current use of longer duration, with relative risks ranging from 1.03 with less than one year of COC use to approximately 1.4 with more than 8-10 years of COC use.

Figure 2: Relevant Studies of Risk of Breast Cancer with Combined Oral Contraceptives

RR = relative risk; OR = odds ratio; HR = hazard ratio. "ever COC" are females with current or past COC use; "never COC use" are females that never used COCs.

The following adverse reactions have been identified during post-approval use of levonorgestrel/ethinyl estradiol tablets and ethinyl estradiol tablets. Because these reactions are reported voluntarily from a population of uncertain size, it is not possible to reliably estimate their frequency or establish a causal relationship to drug exposure.

Gastrointestinal disorders: abdominal distension, vomiting

General disorders and administration site conditions: chest pain, fatigue, malaise, edema peripheral, pain

Immune system disorders: hypersensitivity reaction

Investigations:blood pressure increased

Musculoskeletal and connective tissue disorders: muscle spasms, pain in extremity

Nervous system disorders: dizziness, loss of consciousness

Psychiatric disorders: insomnia

Reproductive and breast disorders: dysmenorrhea

Respiratory, thoracic and mediastinal disorders:pulmonary embolism, pulmonary thrombosis

Skin and subcutaneous tissue disorders: alopecia

Vascular disorders: thrombosis

7. DRUG INTERACTIONS

No drug-drug interaction studies were conducted with AMETHIA tablets.

7.1 Changes in Contraceptive Effectiveness Associated with Co-Administration of Other Products

If a woman on hormonal contraceptives takes a drug or herbal product that induces enzymes, including CYP3A4, that metabolize contraceptive hormones, counsel her to use additional contraception or a different method of contraception. Drugs or herbal products that induce such enzymes may decrease the plasma concentrations of contraceptive hormones, and may decrease the effectiveness of hormonal contraceptives or increase breakthrough bleeding. Some drugs or herbal products that may decrease the effectiveness of hormonal contraceptives include:

- barbiturates
- bosentan
- carbamazepine
- felbamate
- griseofulvin
- oxcarbazepine
- phenytoin
- rifampin
- St. John's wort
- topiramate

HIV protease inhibitors and non-nucleoside reverse transcriptase inhibitors: Significant changes (increase or decrease) in the plasma levels of the estrogen and progestin have been noted in some cases of co-administration of HIV protease inhibitors or with non-nucleoside reverse transcriptase inhibitors.

Antibiotics: There have been reports of pregnancy while taking hormonal contraceptives and antibiotics, but clinical pharmacokinetic studies have not shown consistent effects of antibiotics on plasma concentrations of synthetic steroids.

Consult the labeling of all concurrently-used drugs to obtain further information about interactions with hormonal contraceptives or the potential for enzyme alterations.

7.2 Increase in Plasma Levels of Estradiol Associated with Co-Administered Drugs

Co-administration of atorvastatin and certain COCs containing ethinyl estradiol increase AUC values for ethinyl estradiol by approximately 20%. Ascorbic acid and acetaminophen may increase plasma ethinyl estradiol levels, possibly by inhibition of conjugation. CYP3A4 inhibitors such as itraconazole or ketoconazole may increase plasma hormone levels.

7.3 Concomitant Use with Hepatitis C Vaccine (HCV) Combination Therapy – Liver Enzyme Elevation

Do not co-administer AMETHIA tablets with HCV drug combinations containing ombitasvir/paritaprevir/ritonavir, with or without dasabuvir, due to potential for ALT elevations [see Warnings and Precautions (5.4)] .

7.4 Changes in Plasma Levels of Co-Administered Drugs

COCs containing some synthetic estrogens (e.g., ethinyl estradiol) may inhibit the metabolism of other compounds. COCs have been shown to significantly decrease plasma concentrations of lamotrigine likely due to induction of lamotrigine glucuronidation. This may reduce seizure control; therefore, dosage adjustments of lamotrigine may be necessary. Consult the labeling of the concurrently-used drug to obtain further information about interactions with COCs or the potential for enzyme alterations.

8. USE IN SPECIFIC POPULATIONS

8.1 Pregnancy

There is little or no increased risk of birth defects in women who inadvertently use COCs during early pregnancy. Epidemiologic studies and meta-analyses have not found an increased risk of genital or non-genital birth defects (including cardiac anomalies and limb-reduction defects) following exposure to low dose COCs prior to conception or during early pregnancy.

The administration of COCs to induce withdrawal bleeding should not be used as a test for pregnancy. COCs should not be used during pregnancy to treat threatened or habitual abortion.

Women who do not breastfeed may start COCs no earlier than four to six weeks postpartum.

8.3 Nursing Mothers

When possible, advise the nursing mother to use other forms of contraception until she has weaned her child. Estrogen-containing COCs can reduce milk production in breastfeeding mothers. This is less likely to occur once breastfeeding is well established; however, it can occur at any time in some women. Small amounts of oral contraceptive steroids and/or metabolites are present in breast milk.

8.4 Pediatric Use

Safety and efficacy of AMETHIA tablets have been established in women of reproductive age. Safety and efficacy are expected to be the same for postpubertal adolescents under the age of 18 as for users 18 years and older. Use of AMETHIA tablets before menarche is not indicated.

8.5 Geriatric Use

AMETHIA tablets have not been studied in women who have reached menopause and is not indicated in this population.

8.6 Hepatic Impairment

No studies have been conducted to evaluate the effect of hepatic disease on the disposition of AMETHIA tablets. However, steroid hormones may be poorly metabolized in patients with impaired liver function. Acute or chronic disturbances of liver function may necessitate the discontinuation of COC use until markers of liver function return to normal. [See Contraindications (4)and Warnings and Precautions (5.3)].

8.7 Renal Impairment

No studies have been conducted to evaluate the effect of renal disease on the disposition of AMETHIA tablets.

10. OVERDOSAGE

There have been no reports of serious ill effects from overdose of oral contraceptives, including ingestion by children. Overdosage may cause withdrawal bleeding in females and nausea.

11. DESCRIPTION

AMETHIA tablets are an extended-cycle oral contraceptive consisting of 84 white tablets each containing 0.15 mg of levonorgestrel, a synthetic progestogen and 0.03 mg of ethinyl estradiol, and 7 light blue tablets containing 0.01 mg of ethinyl estradiol.

The structural formulas for the active components are:

Levonorgestrel is chemically 18,19-Dinorpregn-4-en-20-yn-3-one, 13-ethyl-17-hydroxy-, (17α)-, (-)-.

Ethinyl Estradiol is 19-Norpregna-1,3,5(10)-trien-20-yne-3,17-diol, (17α)-.

Each white tablet contains the following inactive ingredients: lactose monohydrate, microcrystalline cellulose, povidone, croscarmellose sodium and magnesium stearate.

Each light blue tablet contains the following inactive ingredients: vitamin E, anhydrous lactose, povidone, FD&C Blue #1, colloidal silicon dioxide, corn starch and stearic acid.

12. CLINICAL PHARMACOLOGY

12.1 Mechanism of action

COCs lower the risk of becoming pregnant primarily by suppressing ovulation. Other possible mechanisms may include cervical mucus changes that inhibit sperm penetration and endometrial changes that reduce the likelihood of implantation.

12.3. Pharmacokinetics

Absorption

Ethinyl estradiol and levonorgestrel are absorbed with maximum plasma concentrations occurring within 2 hours after AMETHIA tablets administration. Levonorgestrel is completely absorbed after oral administration (bioavailability nearly 100%) and is not subject to first- pass metabolism. Ethinyl estradiol is absorbed from the gastrointestinal tract but, due to first-pass metabolism in gut mucosa and liver, the bioavailability of ethinyl estradiol is approximately 43%.

The daily exposure to levonorgestrel and ethinyl estradiol on Day 21, corresponding to the end of a typical 3-week contraceptive regimen, and on Day 84, at the end of an extended cycle regimen, were similar. There was no additional accumulation of ethinyl estradiol after dosing a 0.03 mg ethinyl estradiol tablet during Days 84-91. The mean plasma pharmacokinetic parameters of AMETHIA tablets following a single dose of one levonorgestrel/ethinyl estradiol combination tablet, for 84 days, in normal healthy women are reported in Table 3.

Table 3: Mean Pharmacokinetic Parameters for Levonorgestrel/Ethinyl Estradiol tablets and Ethinyl Estradiol during Daily One Tablet Dosing for 84 Days
 | AUC0-24 hr (mean ± SD) | Cmax (mean ± SD) | Tmax (mean ± SD)
 |  | Levonorgestrel
Day 1 | 18.2 ± 6.1 ng∙hr/mL | 3.0 ± 1.0 ng/mL | 1.3 ± 0.4 hours
Day 21 | 64.4 ± 25.1 ng∙hr/mL | 6.2 ± 1.6 ng/mL | 1.3 ± 0.4 hours
Day 84 | 60.2 ± 24.6 ng∙hr/mL | 5.5 ± 1.6 ng/mL | 1.3 ± 0.3 hours
 |  | Ethinyl Estradiol
Day 1 | 509.3 ± 172.0 pg∙hr/mL | 69.8 ± 26 pg/mL | 1.5 ± 0.3 hours
Day 21 | 837.1 ± 271.2 pg∙hr/mL | 99.6 ± 31 pg/mL | 1.5 ± 0.3 hours
Day 84 | 791.5 ± 215.0 pg∙hr/mL | 91.3 ± 32 pg/mL | 1.6 ± 0.3 hours

The effect of food on the rate and the extent of levonorgestrel and ethinyl estradiol absorption following oral administration of AMETHIA tablets has not been evaluated.

Distribution

The apparent volume of distribution of levonorgestrel and ethinyl estradiol are reported to be approximately 1.8 L/kg and 4.3 L/kg, respectively. Levonorgestrel is about 97.5 - 99% protein-bound, principally to sex hormone binding globulin (SHBG) and, to a lesser extent, serum albumin. Ethinyl estradiol is about 95 - 97% bound to serum albumin. Ethinyl estradiol does not bind to SHBG, but induces SHBG synthesis, which leads to decreased levonorgestrel clearance. Following repeated daily dosing of levonorgestrel/ethinyl estradiol oral contraceptives, levonorgestrel plasma concentrations accumulate more than predicted based on single-dose pharmacokinetics, due in part, to increased SHBG levels that are induced by ethinyl estradiol, and a possible reduction in hepatic metabolic capacity.

Metabolism

Following absorption, levonorgestrel is conjugated at the 17β-OH position to form sulfate and to a lesser extent, glucuronide conjugates in plasma. Significant amounts of conjugated and unconjugated 3α,5β- tetrahydrolevonorgestrel are also present in plasma, along with much smaller amounts of 3α,5α- tetrahydrolevonorgestrel and 16β-hydroxylevonorgestrel. Levonorgestrel and its phase I metabolites are excreted primarily as glucuronide conjugates. Metabolic clearance rates may differ among individuals by several-fold, and this may account in part for the wide variation observed in levonorgestrel concentrations among users.

First-pass metabolism of ethinyl estradiol involves formation of ethinyl estradiol-3-sulfate in the gut wall, followed by 2-hydroxylation of a portion of the remaining untransformed ethinyl estradiol by hepatic cytochrome P-450 3A4 (CYP3A4). Levels of CYP3A4 vary widely among individuals and can explain the variation in rates of ethinyl estradiol hydroxylation. Hydroxylation at the 4-, 6-, and 16-positions may also occur, although to a much lesser extent than 2-hydroxylation. The various hydroxylated metabolites are subject to further methylation and/or conjugation.

Excretion

About 45% of levonorgestrel and its metabolites are excreted in the urine and about 32% are excreted in feces, mostly as glucuronide conjugates. The terminal elimination half-life for levonorgestrel after a single dose of AMETHIA tablets was about 34 hours.

Ethinyl estradiol is excreted in the urine and feces as glucuronide and sulfate conjugates, and it undergoes enterohepatic recirculation. The terminal elimination half-life of ethinyl estradiol after a single dose of AMETHIA tablets was found to be about 18 hours.

Race

The effect of race on the pharmacokinetics of AMETHIA tablets has not been evaluated.

13. NONCLINICAL TOXICOLOGY

13.1. Carcinogenesis, Mutagenesis, Impairment of Fertility

[See Warnings and Precautions (5.2, 5.3)].

14. CLINICAL STUDIES

In a 12-month, multicenter, randomized, open-label clinical trial, 1,006 women aged 18-40 were studied to assess the safety and efficacy of levonorgestrel/ethinyl estradiol tablets and ethinyl estradiol tablets, completing the equivalent of 8,681 28-day cycles of exposure. The racial demographic of those enrolled was: Caucasian (80%), African-American (11%), Hispanic (5%), Asian (2%), and Other (2%). There were no exclusions for body mass index (BMI) or weight. The weight range of those women treated was 91 to 360 lbs., with a mean weight of 156 lbs. Among the women in the trial, 63% were current or recent hormonal contraceptive users, 26% were prior users (who had used hormonal contraceptives in the past but not in the 6 months prior to enrollment), and 11% were new starts. Of treated women, 14.8% were lost to follow-up, 16.3% discontinued due to an adverse event, and 12.9% discontinued by withdrawing their consent.

The pregnancy rate (Pearl Index [PI]) in women aged 18-35 years was 1.34 pregnancies per 100 women-years of use (95% confidence interval 0.54-2.75), based on 7 pregnancies that occurred after the onset of treatment and within 14 days after the last combination pill. Cycles in which conception did not occur, but which included the use of backup contraception, were not included in the calculation of the PI. The PI includes patients who did not take the drug correctly.

16. HOW SUPPLIED/STORAGE AND HANDLING

16.1 How Supplied

AMETHIA tablets, 0.15mg/0.03 mg and 0.01 mg are available in Extended-Cycle Tablet Dispensers (NDC 51862-047-01), each containing a 13-week supply of tablets: 84 white tablets, each containing 0.15 mg of levonorgestrel and 0.03 mg ethinyl estradiol, and 7 light blue tablets each containing 0.01 mg of ethinyl estradiol. The white tablets are round, flat face beveled edge, unscored tablets with WATSONon one side and 268on the other side. The light blue tablets are round, flat face beveled edge, unscored tablets with WATSONon one side and 270on the other side.

Box of 2 Extended-Cycle Tablet Dispensers

NDC 51862-047-91

16.2 Storage Conditions

Store at 20° to 25°C (68° to 77°F) [see USP Controlled Room Temperature].

17. PATIENT COUNSELING INFORMATION

See FDA-Approved Patient Labeling

- Counsel patients that cigarette smoking increases the risk of serious cardiovascular events from COC use, and that women who are over 35 years old and smoke should not use COCs.
- Counsel patients that this product does not protect against HIV-infection (AIDS) and other sexually transmitted diseases.
- Counsel patients on Warnings and Precautions associated with COCs.
- Counsel patients to take one tablet daily by mouth at the same time every day. Instruct patients what to do in the event pills are missed. See WHAT TO DO IF YOU MISS PILLSsection of FDA-Approved Patient Labeling.
- Counsel patients to use a back-up or alternative method of contraception when enzyme inducers are used with COCs.
- Counsel patients who are breastfeeding or who desire to breastfeed that COCs may reduce breast milk production. This is less likely to occur if breastfeeding is well established.
- Counsel any patient who starts COCs postpartum, and who has not yet had a period, to use an additional method of contraception until she has taken a white tablet for 7 consecutive days.
- Counsel patients that amenorrhea may occur. Pregnancy should be considered in the event of amenorrhea, and should be ruled out if amenorrhea is associated with symptoms of pregnancy, such as morning sickness or unusual breast tenderness.

Distributed by:
Mayne Pharma
Greenville, NC 27834

Manufactured by:
Patheon, Inc.
2100 Syntex Court
Mississauga, Ontario L5N 7K9 Canada

FDA-Approved Patient Labeling
Guide for Using
AMETHIA Levonorgestrel/Ethinyl Estradiol Tablets and Ethinyl Estradiol Tablets,
0.15 mg/0.03 mg and 0.01 mg
Revised August 2022
Rx only

WARNING TO WOMEN WHO SMOKE

Do not use AMETHIA tablets if you smoke cigarettes and are over 35. Smoking increases your risk of serious cardiovascular side effects from birth control pills, including death from heart attack, blood clots or stroke. This risk increases with age and the number of cigarettes you smoke.

Birth control pills help to lower the chances of becoming pregnant. They do not protect against HIV infection (AIDS) and other sexually transmitted diseases.

What Are AMETHIA Tablets?

Levonorgestrel/Ethinyl Estradiol tablets and Ethinyl Estradiol tablets are a birth control pill. They contain two female hormones, an estrogen called ethinyl estradiol, and a progestin called levonorgestrel.

How Well Do AMETHIA Tablets Work?

Your chance of getting pregnant depends on how well you follow the directions for taking your birth control pills. The more carefully you follow the directions, the less chance you have of getting pregnant.

Based on the results of a single clinical study lasting 12 months, 1 to 3 women, out of 100 women, may get pregnant during the first year they use AMETHIA tablets.

The following chart shows the chance of getting pregnant for women who use different methods of birth control. Each box on the chart contains a list of birth control methods that are similar in effectiveness. The most effective methods are at the top of the chart. The box on the bottom of the chart shows the chance of getting pregnant for women who do not use birth control and are trying to get pregnant.

How Do I Take AMETHIA Tablets?

1. Take one pill every day at the same time. If you miss pills you could get pregnant. This includes starting the pack late. The more pills you miss, the more likely you are to get pregnant.
2. Many women have spotting or light bleeding, or may feel sick to their stomach during the first few months of taking AMETHIA tablets. If you feel sick to your stomach, do not stop taking the pill. The problem will usually go away. If it doesn't go away, check with your healthcare provider.
3. Missing pills can also cause spotting or light bleeding, even when you take the missed pills later. On the days you take 2 pills to make up for missed pills, you could also feel a little sick to your stomach.
4. If you have trouble remembering to take AMETHIA tablets, talk to your healthcare provider about how to make pill-taking easier or about using another method of birth control.

Beforeyou start taking AMETHIA Tablets

1. Decide what time of day you want to take your pill. It is important to take it at about the same time every day.
2. Look at your Extended-Cycle Tablet Dispenser. Your Tablet Dispenser consists of 3 trays with cards that hold 91 individually sealed pills (a 13-week or 91-day cycle). The 91 pills consist of 84 white and 7 light blue pills. Trays 1 and 2 each contain 28 white pills (4 rows of 7 pills). Tray 3 contains 35 pills consisting of 28 white pills (4 rows of 7 pills) and 7 light blue pills (1 row of 7 pills).
3. Also find:
  - Where on the first tray in the pack to start taking pills (upper left corner at the Start Here arrow) and
  - In what order to take the pills (follow the weeks and arrow).
4. Be sure you have ready at all times another kind of birth control (such as condoms or spermicides), to use as a backup in case you miss pills.

When to Start AMETHIA Tablets

1. Take the first white pill on the Sunday after your period starts, even if you are still bleeding. If your period begins on Sunday, start the first white pill that same day.
2. Use another method of birth control (such as condoms or spermicides) as a back-up method if you have sex anytime from the Sunday you start your first white pill until the next Sunday (first 7 days). If you have been using a different hormonal method of birth control (such as a different pill, the "patch," or the "vaginal ring"), you need to use another method of birth control (such as condoms or spermicides) each time you have sex after stopping your old method of birth control until you have taken levonorgestrel/ethinyl estradiol tablets and ethinyl estradiol tablets for 7 days.

How to Take AMETHIA Tablets

1. Take one pill at the same time every day until you have taken the last pill in the tablet dispenser.
  - Do not skip pills even if you are experiencing spotting or bleeding or feel sick to your stomach (nausea).
  - Do not skip pills even if you do not have sex very often.
2. When you finish a tablet dispenser
  - After taking the last light blue pill, start taking the first white pill from a new Extended-Cycle Tablet Dispenser the very next day (this should be on a Sunday) regardless of when your period started.
3. If you miss your scheduled period when you are taking the light blue pills, contact your healthcare provider because you may be pregnant. If you are pregnant, you should stop taking AMETHIA tablets.

What To Do If You Miss Pills

If you MISS 1white pill:

1. Take it as soon as you remember. Take the next pill at your regular time. This means you may take 2 pills in 1 day.
2. You do not need to use a back-up birth control method if you have sex.

If you MISS 2white pills in a row:

1. Take 2 pills on the day you remember, and 2 pills the next day.
2. Then take 1 pill a day until you finish the pack.
3. You could become pregnant if you have sex in the 7 days after you miss two pills. You MUST use another birth control method (such as condoms or spermicide) as a back-up for the 7 days after you restart your pills.

If you MISS 3 OR MOREwhite pills in a row:

1. Do not take the missed pills. Keep taking 1 pill every day as indicated on the pack until you have completed all of the remaining pills in the pack. For example: If you resume taking the pill on Thursday, take the pill under "Thursday" and do not take the missed pills. You may experience bleeding during the week following the missed pills.
2. You could become pregnant if you have sex during the days of missed pills or during the first 7 days after restarting your pills.
3. You MUST use a non-hormonal birth control method (such as condoms or spermicide) as a back-up when you miss pills and for the first 7 days after you restart your pills. If you do not have your period when you are taking the light blue pills, call your healthcare provider because you may be pregnant.

If you MISS ANYof the 7 light blue pills:

1. Throw away the missed pills.
2. Keep taking the scheduled pills until the pack is finished.
3. You do not need a back-up method of birth control.

Finally, if you are still not sure what to do about the pills you have missed

1. Use a back-up method anytime you have sex.
2. Keep taking one pill each day until you contact your healthcare provider.

Who Should Not Take AMETHIA Tablets?

Your healthcare provider will not give you AMETHIA tablets if you have:

- Ever had breast cancer or any cancer that is sensitive to female hormones
- Liver disease, including liver tumors
- Been prescribed any Hepatitis C drug combination containing ombitasvir/paritaprevir/ritonavir, with or without dasabuvir. This may increase levels of the liver enzyme "alanine aminotransferase" (ALT) in the blood
- Ever had blood clots in your arms, legs, or lungs
- Ever had a stroke
- Ever had a heart attack
- Certain heart valve problems or heart rhythm abnormalities that can cause blood clots to form in the heart
- An inherited problem with your blood that makes it clot more than normal
- High blood pressure that medicine can't control
- Diabetes with kidney, eye, or blood vessel damage
- Certain kinds of severe migraine headaches with aura, numbness, weakness or changes in vision

Also, do not take birth control pills if you:

- Smoke and are over 35 years old
- Are pregnant

Birth control pills may not be a good choice for you if you have ever had jaundice (yellowing of the skin or eyes) caused by pregnancy.

What Else Should I Know About Taking AMETHIA Tablets?

Birth control pills do notprotect you against any sexually transmitted disease, including HIV, the virus that causes AIDS.

Do not skip any pills, even if you do not have sex often.

Birth control pills should not be taken during pregnancy. However, birth control pills taken by accident during pregnancy are not known to cause birth defects.

If you are breastfeeding, consider another birth control method until you are ready to stop breastfeeding. Birth control pills that contain estrogen, like AMETHIA tablets, may decrease the amount of milk you make. A small amount of the pill's hormones pass into breast milk.

Tell your healthcare provider about all medicines and herbal products that you take. Some medicines and herbal products may make birth control pills less effective, including:

- barbiturates
- bosentan
- carbamazepine
- felbamate
- griseofulvin
- oxcarbazepine
- phenytoin
- rifampin
- St. John's wort
- topiramate

Consider using another birth control method when you take medicines that may make birth control pills less effective.

Birth control pills may interact with lamotrigine, an anticonvulsant used for epilepsy. This may increase the risk of seizures, so your physician may need to adjust the dose of lamotrigine.

If you have vomiting or diarrhea, your birth control pills may not work as well. Use another birth control method, like condoms or a spermicide, until you check with your healthcare provider.

What Are The Most Serious Risks Of Taking Birth Control Pills?

Like pregnancy, birth control pills increase the risk of serious blood clots, especially in women who have other risk factors, such as smoking, obesity, or age > 35. It is possible to die from a problem caused by a blood clot, such as a heart attack or a stroke. Some examples of serious blood clots are blood clots in the:

- Legs (thrombophlebitis)
- Lungs (pulmonary embolus)
- Eyes (loss of eyesight)
- Heart (heart attack)
- Brain (stroke)

Women who take birth control pills may get:

- High blood pressure
- Gallbladder problems
- Rare cancerous or noncancerous liver tumors

All of these events are uncommon in healthy women.

Call your healthcare provider right away if you have:

- Persistent leg pain
- Sudden shortness of breath
- Sudden blindness, partial or complete
- Severe pain in your chest
- Sudden, severe headache unlike your usual headaches
- Weakness or numbness in an arm or leg, or trouble speaking
- Yellowing of the skin or eyeballs

What Are Common Side Effects Of Birth Control Pills?

The most common side effects of birth control pills are:

- Spotting or bleeding between menstrual periods
- Nausea
- Breast tenderness
- Headache

These side effects are usually mild and usually disappear with time.

Less common side effects are:

- Acne
- Less sexual desire
- Bloating or fluid retention
- Blotchy darkening of the skin, especially on the face
- High blood sugar, especially in women who already have diabetes
- High fat levels in the blood
- Depression, especially if you have had depression in the past. Call your healthcare provider immediately if you have any thoughts of harming yourself.
- Problems tolerating contact lenses
- Weight changes

This is not a complete list of possible side effects. Talk to your healthcare provider if you develop any side effects that concern you. You may report side effects to the FDA at 1-800-FDA-1088.

No serious problems have been reported from a birth control pill overdose, even when accidentally taken by children.

Do Birth Control Pills Cause Cancer?

It is not known if hormonal birth control pills cause breast cancer. Some studies, but not all, suggest that there could be a slight increase in the risk of breast cancer among current users with longer duration of use.

If you have breast cancer now, or have had it in the past, do not use hormonal birth control because some breast cancers are sensitive to hormones. Women who use birth control pills may have a slightly higher chance of getting cervical cancer. However, this may be due to other reasons such as having more sexual partners.

What Should I Know About My Period When Taking AMETHIA tablets?

When you take AMETHIA tablets, which have a 91-day extended dosing cycle, you should expect to have 4 scheduled periods per year (bleeding when you are taking the 7 light blue pills). Each period is likely to last about 3 days. However, you will probably have more bleeding or spotting between your scheduled periods than if you were using a birth control pill with a 28-day dosing cycle. During the first AMETHIA tablets 91-day treatment cycle, about 3 in 10 women may have 20 or more days of unplanned bleeding or spotting. This bleeding or spotting tends to decrease with time. Do not stop taking AMETHIA tablets because of this bleeding or spotting. If the spotting continues for more than 7 consecutive days or if the bleeding is heavy, call your healthcare provider.

What If I Miss My Scheduled Period When Taking AMETHIA tablets?

You should consider the possibility that you are pregnant if you miss your scheduled period (no bleeding on the days that you are taking light blue tablets). Since scheduled periods are less frequent when you are taking AMETHIA tablets, notify your healthcare provider that you have missed your period and that you are taking AMETHIA tablets. Also notify your healthcare provider if you have symptoms of pregnancy such as morning sickness or unusual breast tenderness. It is important that your healthcare provider evaluates you to determine if you are pregnant. Stop taking AMETHIA tablets if it is determined that you are pregnant.

What If I Want To Become Pregnant?

You may stop taking the pill whenever you wish. Consider a visit with your healthcare provider for a pre-pregnancy checkup before you stop taking the pill.

General Advice About AMETHIA tablets

Your healthcare provider prescribed AMETHIA tablets for you. Do not share AMETHIA tablets with anyone else. Keep AMETHIA tablets out of the reach of children.

If you have concerns or questions, ask your healthcare provider. You may also ask your healthcare providers for a more detailed label written for medical professionals.

Distributed by:
Mayne Pharma
Greenville, NC 27834

Manufactured by:
Patheon Inc.
2100 Syntex Court
Mississauga, Ontario L5N 7K9
Canada

Revised: August 2022

PRINCIPAL DISPLAY PANEL - Kit Carton

NDC 51862-047-91

Amethia™
(Levonorgestrel/Ethinyl Estradiol Tablets
and Ethinyl Estradiol Tablets,
0.15 mg/0.03 mg and 0.01 mg)

Contains 2 Extended-Cycle Tablet Dispensers, each containing 91 tablets: 84 white tablets,
each containing 0.15 mg levonorgestrel with 0.03 mg ethinyl estradiol, and 7 light blue
tablets, each containing 0.01 mg ethinyl estradiol.

Rx only

2 Extended-Cycle Tablet Dispensers, 91 Tablets Each

maynepharma